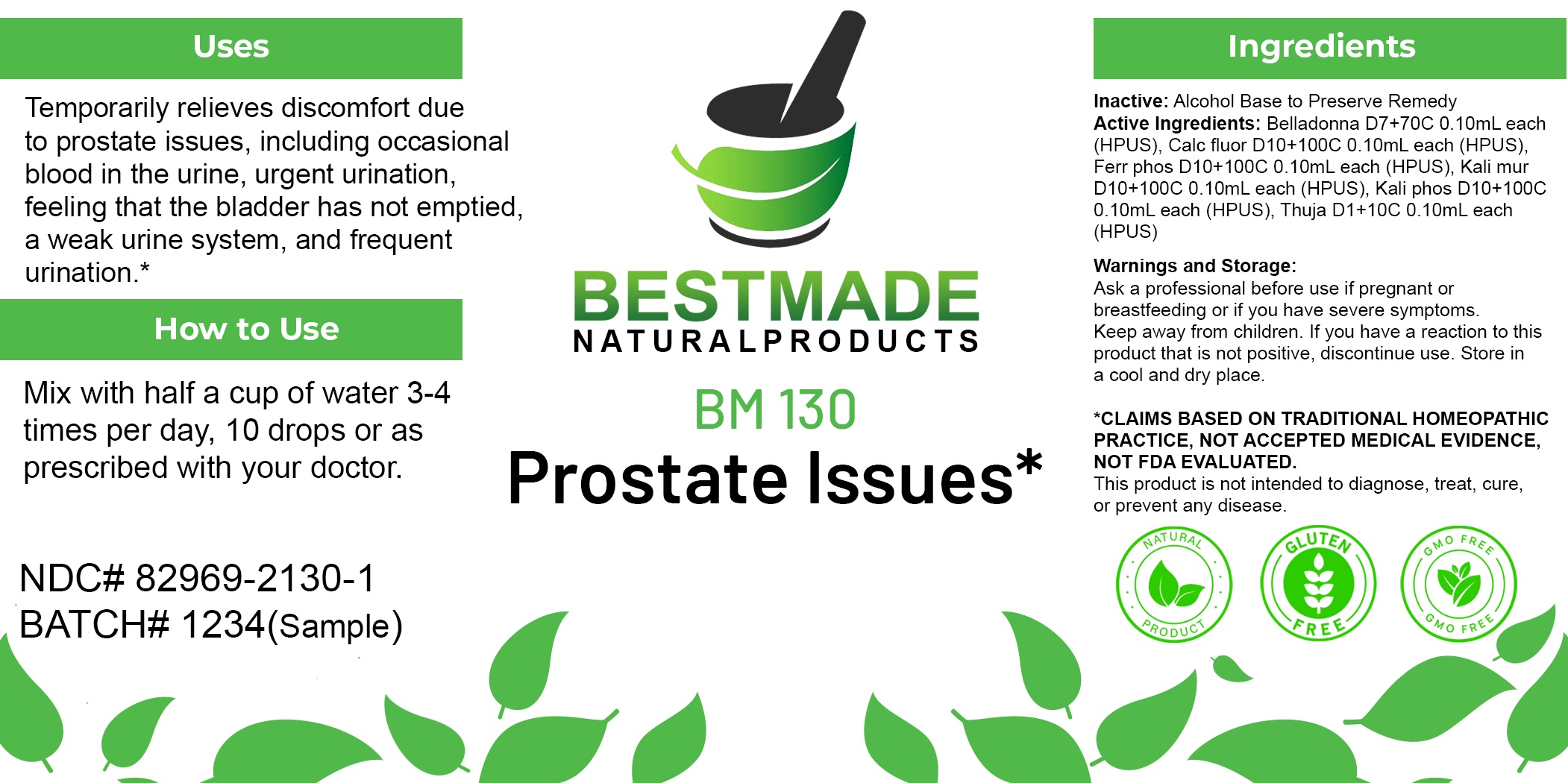 DRUG LABEL: Bestmade Natural Products BM130
NDC: 82969-2130 | Form: LIQUID
Manufacturer: Bestmade Natural Products
Category: homeopathic | Type: HUMAN OTC DRUG LABEL
Date: 20250210

ACTIVE INGREDIENTS: DIBASIC POTASSIUM PHOSPHATE 30 [hp_C]/30 [hp_C]; CALCIUM FLUORIDE 30 [hp_C]/30 [hp_C]; POTASSIUM CHLORIDE 30 [hp_C]/30 [hp_C]; ATROPA BELLADONNA 30 [hp_C]/30 [hp_C]; FERROSOFERRIC PHOSPHATE 30 [hp_C]/30 [hp_C]; THUJA OCCIDENTALIS LEAFY TWIG 30 [hp_C]/30 [hp_C]
INACTIVE INGREDIENTS: ALCOHOL 30 [hp_C]/30 [hp_C]

BM130

DOSAGE AND ADMINISTRATION

How to Use

Mix with half a cup of water 3-4 times per day. Ages 12 or older, 10 drops. Ages 12-2, 5 drops. Ages 2 and under, consult your Doctor.

Inactive:

Alcohol Base to Preserve Product

ACTIVE INGREDIENTS

Belladonna D7+70C 0.10mL each (HPUS), Calc fluor D10+100C 0.10mL each (HPUS), Ferr phos D10+100C 0.10mL each (HPUS), Kali mur D10+100C 0.10mL each (HPUS), Kali phos D10+100C 0.10mL each (HPUS), Thuja D1+10C 0.10mL each (HPUS)

Uses
Temporarily relieves discomfort due to prostate issues, including occasional blood in the urine, urgent urination, feeling that the bladder has not emptied, a weak urine system, and frequent urination.*

Uses
Temporarily relieves discomfort due to prostate issues, including occasional blood in the urine, urgent urination, feeling that the bladder has not emptied, a weak urine system, and frequent urination.*

KEEP OUT OF REACH OF CHILDREN

Warnings and Storage:

Ask a professional before use if pregnant or breastfeeding or if you have severe symptoms.

Keep away from children. If you have a reaction to this product that is not positive, discontinue use. Store in a cool and dry place

*CLAIMS BASED ON TRADITIONAL HOMEOPATHIC PRACTICE, NOT ACCEPTED MEDICAL EVIDENCE NOT FDA EVALUATED.
This product is not intended to diagnose, treat, cure, or prevent any disease.

Warnings and Storage:

Ask a professional before use if pregnant or breastfeeding or if you have severe symptoms.

Keep away from children. If you have a reaction to this product that is not positive, discontinue use. Store in a cool and dry place

*CLAIMS BASED ON TRADITIONAL HOMEOPATHIC PRACTICE, NOT ACCEPTED MEDICAL EVIDENCE NOT FDA EVALUATED.
This product is not intended to diagnose, treat, cure, or prevent any disease.

Entire package label